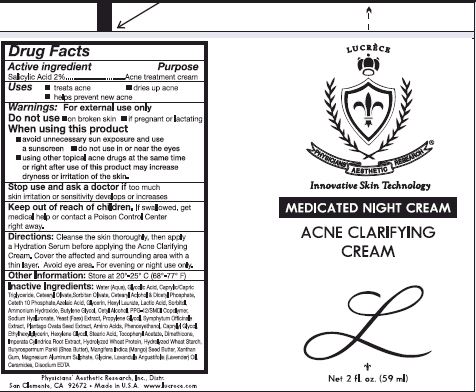 DRUG LABEL: Acne Clarifying Cream
NDC: 62742-4113 | Form: CREAM
Manufacturer: Allure Labs, Inc
Category: otc | Type: HUMAN OTC DRUG LABEL
Date: 20171204

ACTIVE INGREDIENTS: SALICYLIC ACID 20 mg/1 mL
INACTIVE INGREDIENTS: WATER; GLYCOLIC ACID; MEDIUM-CHAIN TRIGLYCERIDES; CETEARYL OLIVATE; SORBITAN OLIVATE; CETOSTEARYL ALCOHOL; DIHEXADECYL PHOSPHATE; CETETH-10 PHOSPHATE; AZELAIC ACID; GLYCERIN; HEXYL LAURATE; LACTIC ACID; SORBITOL; AMMONIA; BUTYLENE GLYCOL; CETYL ALCOHOL; PPG-12/SMDI COPOLYMER; HYALURONATE SODIUM; YEAST; PROPYLENE GLYCOL; SYMPHYTUM OFFICINALE WHOLE; PLANTAGO OVATA SEED; AMINO ACIDS; PHENOXYETHANOL; CAPRYLYL GLYCOL; ETHYLHEXYLGLYCERIN; HEXYLENE GLYCOL; STEARIC ACID; .ALPHA.-TOCOPHEROL ACETATE; DIMETHICONE; IMPERATA CYLINDRICA ROOT; HYDROLYZED WHEAT PROTEIN (ENZYMATIC, 3000 MW); SHEA BUTTER; MANGIFERA INDICA SEED BUTTER; XANTHAN GUM; GLYCINE; LAVENDER OIL; CERAMIDE 1; EDETATE DISODIUM

Drug Facts

ACTIVE INGREDIENT

Salicylic Acid 2%

PURPOSE

Acne Treatment Cream

INDICATIONS AND USAGE

Uses: Treats Acne, dries up Acne, helps prevent new acne

WARNINGS

For external use only

do not use:

on a broken skin

if pregnant or lactating

when using this product:

avoid unnecessary sun exposure and use a sunscreen

do not use in or near the eyes

using other acne topical drugs at the same time or right after use of this product may increase dryness or irritation of the skin

stop use and ask a doctor if too much irritation or sensitivity developes or increases

KEEP OUT OF REACH OF CHILDREN

if swallowed, get medical help or contact a Poison Control Center right away

DOSAGE AND ADMINISTRATION

Directions: Cleanse the skin thoroughly, then apply a hydration serum before applying the acne clarifying cream. Cover the affected and surrounding area with a thin layer. Avoid eye area. For evening or night use only

OTHER SAFETY INFORMATION

Store at 20-25 C (68-77 F)

INACTIVE INGREDIENT

Water (Aqua), Glycolic Acid, Caprylic/Capric triglyceride, Cetearyl Olivate, Sorbitan Olivate, Cetearyl Alcohol and Dicetyl Phospahte, Ceteth 10 Phosphate, Azelaic Acid, Glycerin, Hexyl Laurate, Lactic Acid, Sorbitol, Ammonium Hydroxide, Butylene Glycol, Cetyl Alcohol, PPG-12/SMDI Copolymer, Sodium Hyaluronate, Yeast (Faex) Extract, Propylene Glycol, Symphytum Officinale Extract, Plantago Ovata Seed Extract, Amino Acids, Phenoxyethanol, Caprylyl Glycol, Ethylhexylglycerin, Hexylene Glycol, Stearic Acid, Tocopheryl Acetate, Dimethicone, Imperata Cylindrica Root Extract, Hydrolyzed Wheat Protein, Hydrolyzed Wheat Starch, Butyrospermum Parkii (Shea Butter), Mangifera Indica (Mango) Seed Butter, Xanthan Gum, Magnisium Aluminium Sulphate, Glycine, Lavandula Angustifolia (Lavender)Oil, Ceramides, Disodium EDTA

PACKAGE LABEL

Physicians Aesthetic Research, Inc., Distr.

San Clemente, CA 92672

Made in U.S.A.

www.lucrece.com